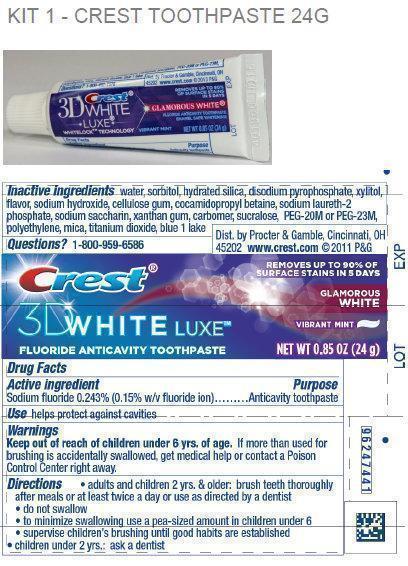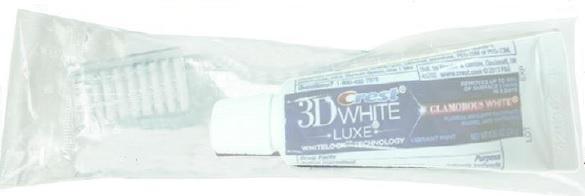 DRUG LABEL: Crest
NDC: 69491-831 | Form: PASTE, DENTIFRICE
Manufacturer: Buzz Export Services Pty., Ltd.
Category: otc | Type: HUMAN OTC DRUG LABEL
Date: 20210503

ACTIVE INGREDIENTS: SODIUM FLUORIDE 1.5 mg/1 g
INACTIVE INGREDIENTS: WATER; SORBITOL; HYDRATED SILICA; SODIUM PHOSPHATE, DIBASIC, ANHYDROUS; XYLITOL; SODIUM HYDROXIDE; COCAMIDOPROPYL BETAINE; SODIUM LAURETH-2 PHOSPHATE; SACCHARIN SODIUM; XANTHAN GUM; SUCRALOSE; POLYETHYLENE OXIDE 900000; HIGH DENSITY POLYETHYLENE; MICA; TITANIUM DIOXIDE; FD&C BLUE NO. 1

Dental Kit - Crest Toothpaste

Active Ingredient

Sodium fluoride 0.243% (0.15% w/v fluoride ion)

Purpose

Anticavity toothpaste

Use

helps protect against cavities

Keep out of reach of children under 6 yrs. of age.

If more than used for brushing is accidentally swallowed, get medical help or contact a Poison Control Center right away.

Directions

- adults and children 2 yrs. & older: brush teeth thoroughly after meals or at least twice a day or use as directed by a dentist
- do not swallow
- to minimize swallowing use a pea-sized amount in children under 6
- supervise children's brushing until good habits are established
- children under 2 yrs.: ask a dentist

Inactive Ingredients

water, sorbitol, hydrated silica, disodium pyrophosphate, xylitol, flavor, sodium hydroxide, cellulose gum, cocamidopropyl betaine, sodium laureth-2 phosphate, sodium saccharin, xanthan gum, carbomer, sucralose, polyethylene oxide, polyethylene, mica, titanium dioxide, blue 1 lake

Questions?

1-800-959-6586

Dist. by Procter & Gamble, Cincinnati, OH 45202

Package Labeling

Kit Package: